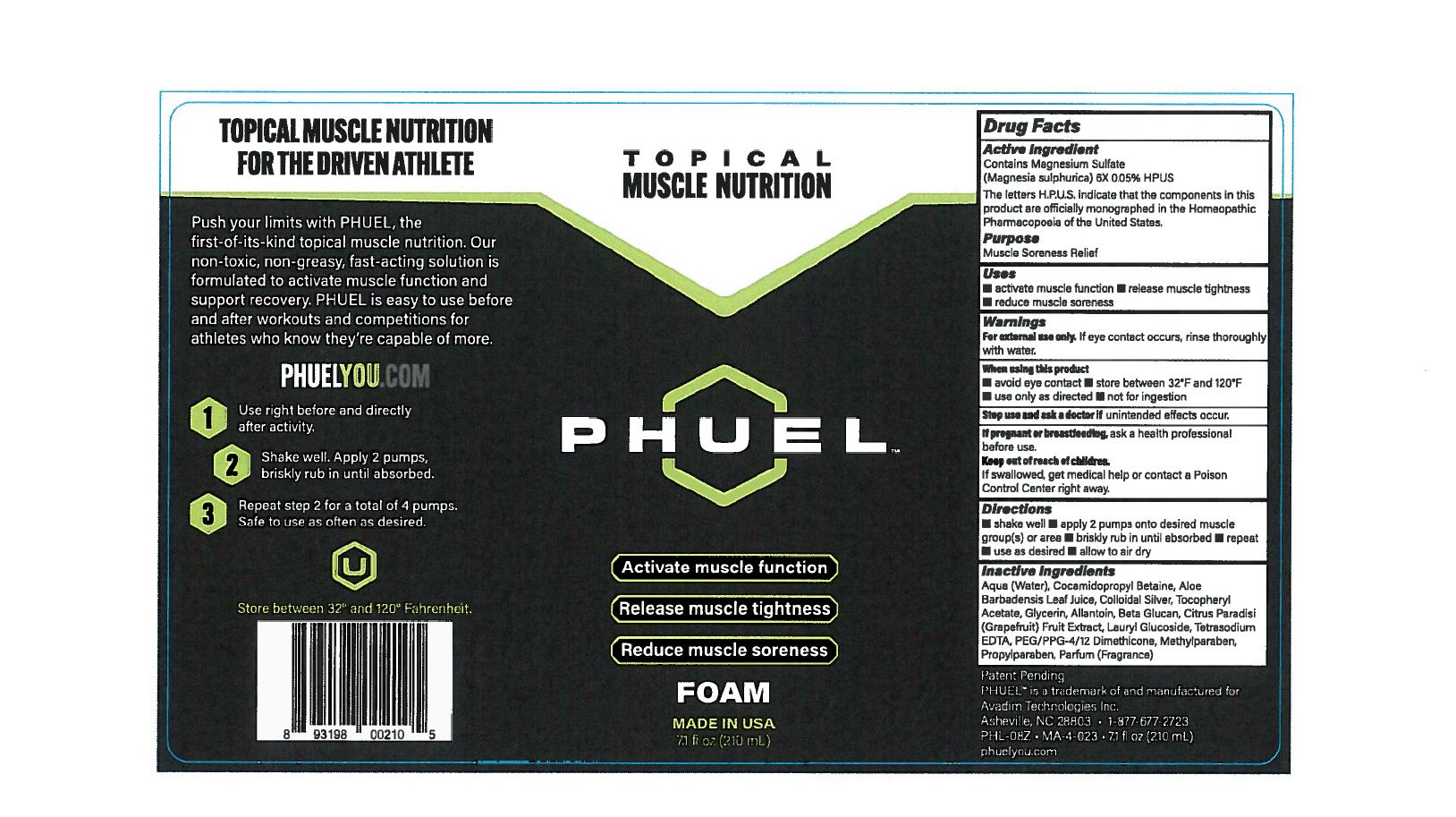 DRUG LABEL: PHUEL
NDC: 71064-0010 | Form: SOLUTION
Manufacturer: Relion Manufacturing
Category: homeopathic | Type: HUMAN PRESCRIPTION DRUG LABEL
Date: 20210426

ACTIVE INGREDIENTS: MAGNESIUM SULFATE HEPTAHYDRATE 6 [hp_X]/1 mL
INACTIVE INGREDIENTS: METHYLPARABEN

Phuel Foam